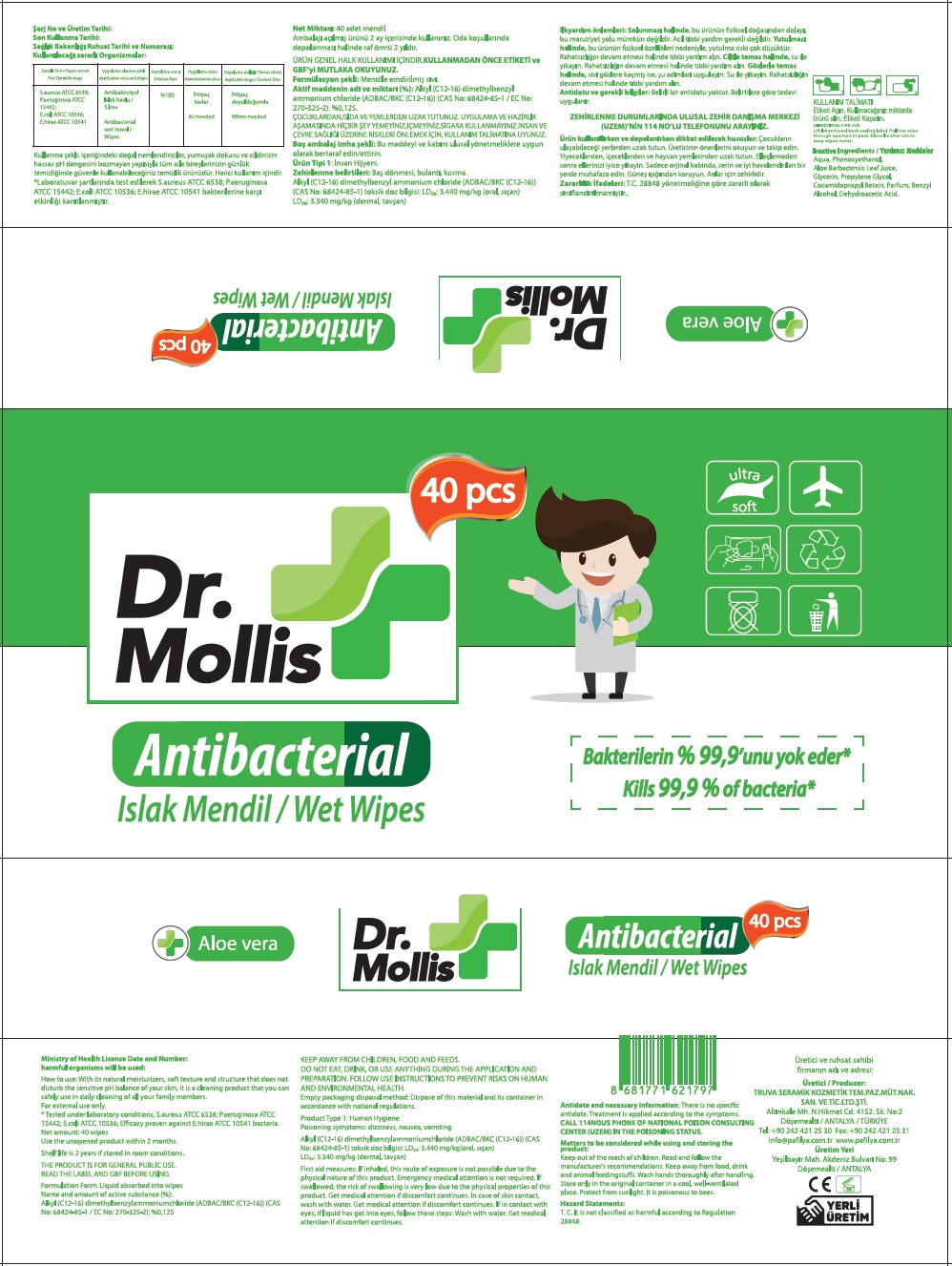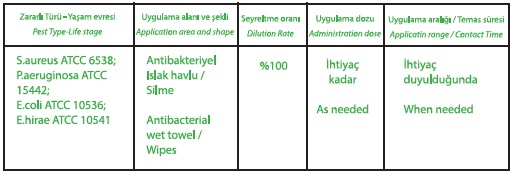 DRUG LABEL: Dr.Mollis
NDC: 79259-012 | Form: CLOTH
Manufacturer: TRUVA SERAMIK KOZMETIK TEMIZLIK PAZARLAMA MUTEAHHITLIK NAKLIYAT SANAYI VE TICARET LTD STI
Category: otc | Type: HUMAN OTC DRUG LABEL
Date: 20200706

ACTIVE INGREDIENTS: BENZALKONIUM CHLORIDE 0.125 g/100 mL
INACTIVE INGREDIENTS: WATER; PHENOXYETHANOL; ALOE VERA LEAF; GLYCERIN; PROPYLENE GLYCOL; COCAMIDOPROPYL BETAINE; BENZYL ALCOHOL; DEHYDROACETIC ACID

Dr. Mollis Antibacterial Wet Wipes

Name and amount of active substance (%):

Alkyl (C12-16) dimethylbenzylammoniumchloride (ADBAC/BKC (C12-16)) (CAS No: 68424-85-1 / EC No: 270-325-2): %0.125

Purpose: Antibacterial

INDICATIONS AND USAGE

Use: Decreases bacteria on the skin

WARNINGS

DO NOT EAT, DRINK OR USE ANYTHING DURING THE APPLICATION AND PREPARATION.

FOLLOW USE INSTRUCTIONS TO PREVENT RISK ON HUMAN AND ENVIRONMENTAL HEALTH.

KEEP AWAY FROM CHILDREN, FOOD and

DIRECTIONS FOR USE

Lift lid and peel back sealing label. Pull top wipe through aperture in pack. Close lid after use to keep wipes moist.

Other Information: Use the unopened product within 2 months.

Shelf life is 2 years if stored in room conditions.

Inactive Ingredients

Aqua, Phenoxyethanol, Aloe Barbadensis Leaf juice, Glycerin, Propylene Glycol, Cocamidopropyl Betaine, Parfum, Benzyl Alcohol, Dehydroacetic Acid.

Ministry of Health License Date and Number:

harmful organisms will be used:

How to use: With its natural moisturizers, soft texture and structure that does not disturb the sensitive pH balance of your skin, it is a cleaning product that you can safely use in daily cleaning of all your family members.

* Tested under laboratory conditions, S.aureus ATCC 6538; P.aeruginosa ATCC 15442; E.coli ATCC 10536; Efficacy proven against E.hirae ATCC 10541 bacteria.

THE PRODUCT IS FOR GENERAL PUBLIC USE.

READ THE LABEL AND GBF BEFORE USING.

Formulation Form: Liquid absorbed into wipes

Empty packaging disposal method: Dispose of this material and its container in accordance with national regulations.

Product Type 1: Human Hygiene

Poisoning symptoms: dizziness, nausea, vomiting

Alkyl (C12-16) dimethylbenzylammoniumchloride (ADBAC/BKC (C12-16)) (CAS No: 68424-85-1) toksik doz bilgisi: LD50: 3.440 mg/kg(oral, sican) LD50: 3.440 mg/kg (dermal, tavsan)

First aid measures: If inhaled, this route of exposure is not possible due to the physical nature of this product. Emergency medical attention is not required. If swallowed, the risk of swallowing is very low due to the physical properties of this product. Get medical attention if discomfort continues. In case of skin contact, wash with water. Get medical attention if discomfort continues. If in contact with eyes, if liquid has got into eyes, follow these steps: Wash with water. Get medical attention if discomfort continues.

Antidote and necessary information: There is no specific antidote. Treatment is applied according to the symptoms.

CALL 114NOUS PHONE OF NATIONAL POISON CONSULTING CENTER (UZEM) IN THE POISONING STATUS.

Matters to be considered while using and storing the product:

Keep out of the reach of children. Read and follow the manufacturer's recommendations. Keep away from food, drink and animal feedingstuffs. Wash hands thoroughly after handling. Store only in the original container in a cool, well-ventilated place. Protect from sunlight. It is poisonous to bees.

Hazard Statements:

T. C. It is not classified as harmful according to Regulation 28848.

Üretici / Producer:

TRUVA SERAMIK KOZMETIK TEM. PAZ. MÜT.NAK.SAN.TIC.LTD.ŞTI.

Altınkale Mh. N. Hikmet Cd. 4152. Sk. No:2

Döşemealti / ANTALYA / TÜRKİYE

Tel: +90 242 421 25 30 Fax: +90 242 421 25 31

info@pafilya.com.tr www.pafilya.com.tr

Üretim Yeri

yeşilbayir Mah. Akdeniz Bulvari No: 99

Döşemealti / ANTALYA